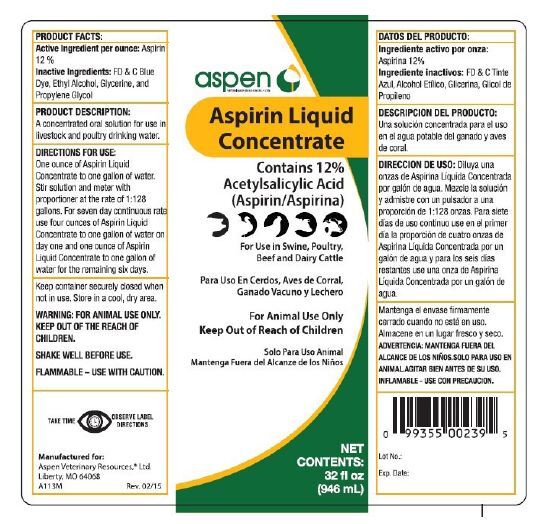 DRUG LABEL: Aspen Aspirin Liquid Concentrate
NDC: 65090-111 | Form: LIQUID
Manufacturer: AHC Products Inc
Category: animal | Type: OTC ANIMAL DRUG LABEL
Date: 20230710

ACTIVE INGREDIENTS: ASPIRIN 120 mg/1 mL
INACTIVE INGREDIENTS: FD&C BLUE NO. 1 1300 ng/1 mL; GLYCERIN 4.9 mg/1 mL; PROPYLENE GLYCOL 139 mg/1 mL; ALCOHOL 706 mg/1 mL; ETHYL ACETATE 30 mg/1 mL

WARNINGS AND PRECAUTIONS

For Animal Use Only
Keep Out of Reach of Children
Solo Para Uso Animal
Mantenga Fuera del Alcanze de los Ninos

WARNINGS: FOR ANIMAL USE ONLY. KEEP OUT OF THE REACH OF CHILDREN. SHAKE WELL BEFORE USE. FLAMMABLE-USE WITH CAUTION.

ADVERTENCIA: ANIMAL SOLO PARA USO. Mantener fuera del alcance de los ninos. AGITAR BIEN ANTES DE SU USO. INFLAMABLES: USO CON PRECAUCION.

INDICATIONS AND USAGE

A concentrated oral solution for use in livestock and poultry drinking water.

A solucion oral para uso concentrada en agua potable de ganado y aves de corral.

DOSAGE AND ADMINISTRATION

One ounce of Aspirin Liquid Concentrate to one gallon of water. Stir solution and meter with proportioner at the rate of 1:128 gallons. For seven day continuous rate use four ounces of Aspirin Liquid Concentrate to one gallon of water on day one and one ounce of Aspirin Liquid Concentrate to one gallon of water for the remaining six days.

Keep container securely closed when not in use. Store in a cool, dry place.

Una onza de Aspirina Liquida Concentrada para un galon de agua. Agitar la solucion y medidor con dosificador a una tasa de 1:128 galones. Para siete dias continuos tasa utilizar cuatro onzas de Aspirina Liquida Concentrada para un galon de agua en el primer dia y una onza de Aspirina Liquida Concentrada para un galon de agua para los restantes sies dias.
Conservese el recipiente cerrado de forma segura cuando no este en uso. Almacenar en un lugar fresco y seco.

Active Ingredient per ounce: Aspirin 12%

Ingrediente activo por onza: Aspirina 12%

INACTIVE INGREDIENT

Inactive Ingredients: FD & C Blue Dye, Ethyl Alcohol, Glycerine, and Propylene Glycol

Ingredientes inactivos: FD & C azul el tinte, Alcohol etílico, Glicerina, Glicol de propileno

PACKAGE LABEL

ASPEN Aspirin Liquid Concentrate
Contains 12% Acetylsalicylic Acid (Aspirin/Aspirina
For use in Swine, Poultry, Beef and Dairy Cattle
Para Uso Cerdos, Aves de Corral, Ganado Vacuno y Lechero

NET CONTENTS 32 fl oz (946 mL)

Add image transcription here...